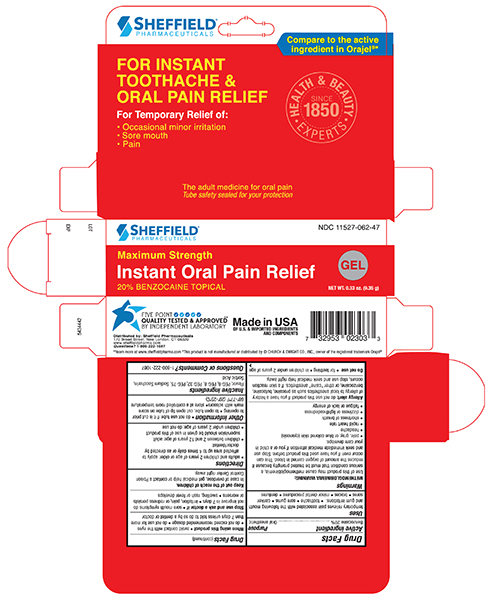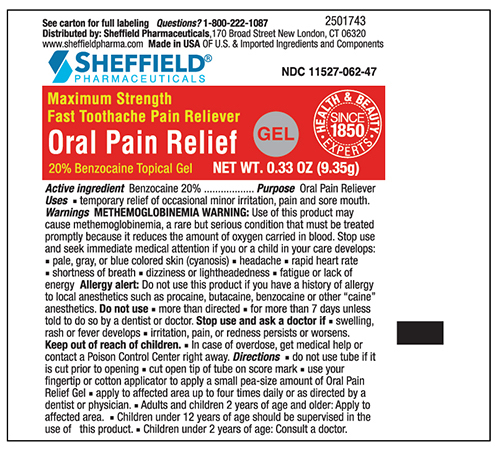 DRUG LABEL: Sheffield Pain Relief
NDC: 11527-062 | Form: GEL
Manufacturer: Sheffield Pharmaceuticals LLC
Category: otc | Type: HUMAN OTC DRUG LABEL
Date: 20250219

ACTIVE INGREDIENTS: BENZOCAINE 200 mg/1 g
INACTIVE INGREDIENTS: POLYETHYLENE GLYCOL 300; POLYETHYLENE GLYCOL 400; POLYETHYLENE GLYCOL 1500; POLYETHYLENE GLYCOL 3350; Saccharin Sodium; Sorbic Acid

Drug Facts

Active Ingredient

Benzocaine 20%

Purpose

Oral Pain Reliever

Uses

- temporary relief of occasional minor irritation, pain and sore mouth

Warnings

Allergy alert: Do not use this product if you have a history of allergy to local anesthetics such as procaine, butacaine, benzocaine or other "caine" anesthetics.

Do not use

- more than directed
- for more than 7 days unless told to do so by a dentist or doctor

Stop use and ask a doctor if

- swelling, rash or fever develops
- irritation, pain, or redness persists or worsens

Keep out of reach of children. In case of overdose, get medical help or contact a Poison Control Center right away.

Directions

- do not use tube if it is cut prior to opening
- cut open tip of tube on score mark
- use your fingertip or cotton applicator to apply a small pea-size amount of Oral Pain Relief Gel
- apply to affected area up to four times daily or as directed by a dentist or physician
- Adults and children 2 years of age and older: Apply to affected area
- Children under 12 years of age should be supervised in the use of this product
- Children under 2 years of age: Consult a doctor

Other information

- store at a controlled room temperature 59°-86°F (15°-30°C)

Inactive ingredients

Flavor, PEG 540, PEG 6, PEG 75, PEG 8, Sodium Saccharin, Sorbic Acid

Principal Display Panel – 0.33oz Carton Label

Sheffield Pharmaceuticals NDC 11527-062-47

Oral Pain Relief

Maxium Strength GEL

Fast Toothache Pain Reliever

20% Benzocaine Topical Gel

NET WT. 0.33 OZ (9.35g)

Made in the USA